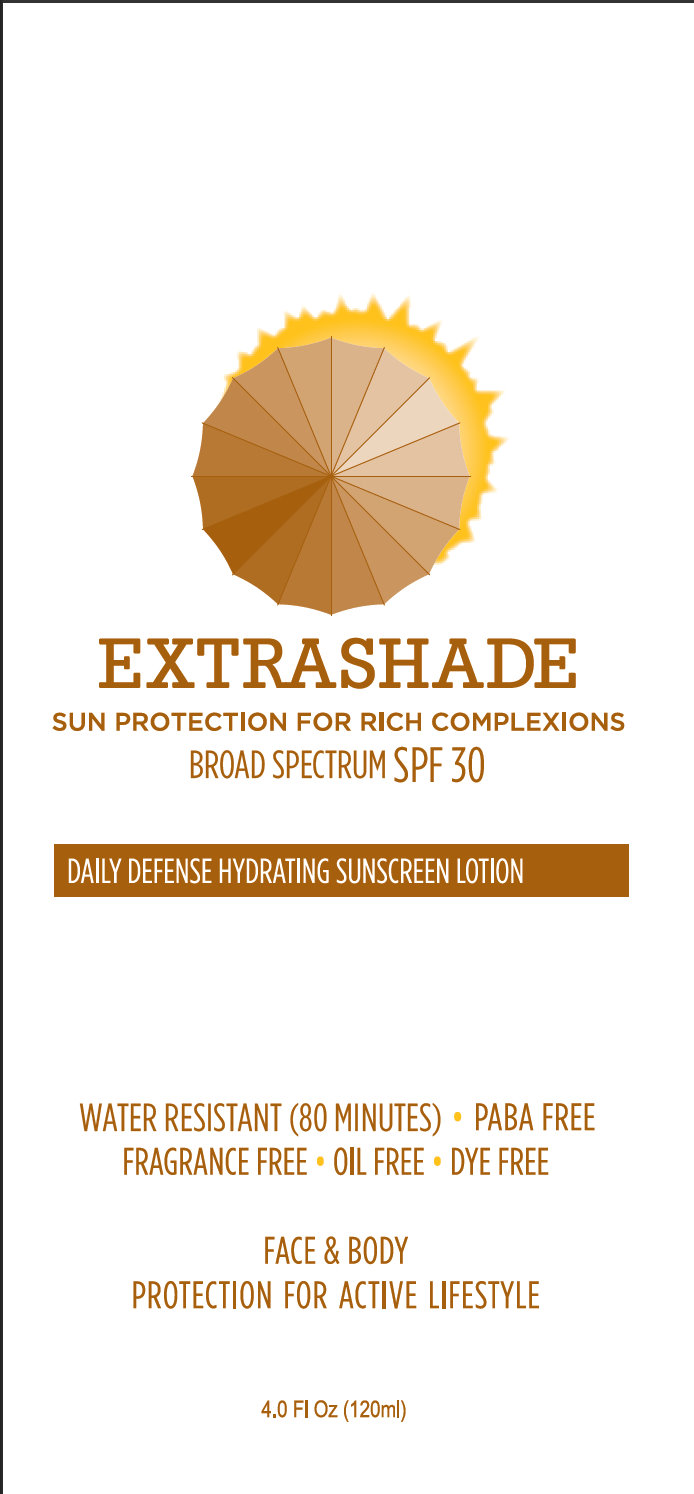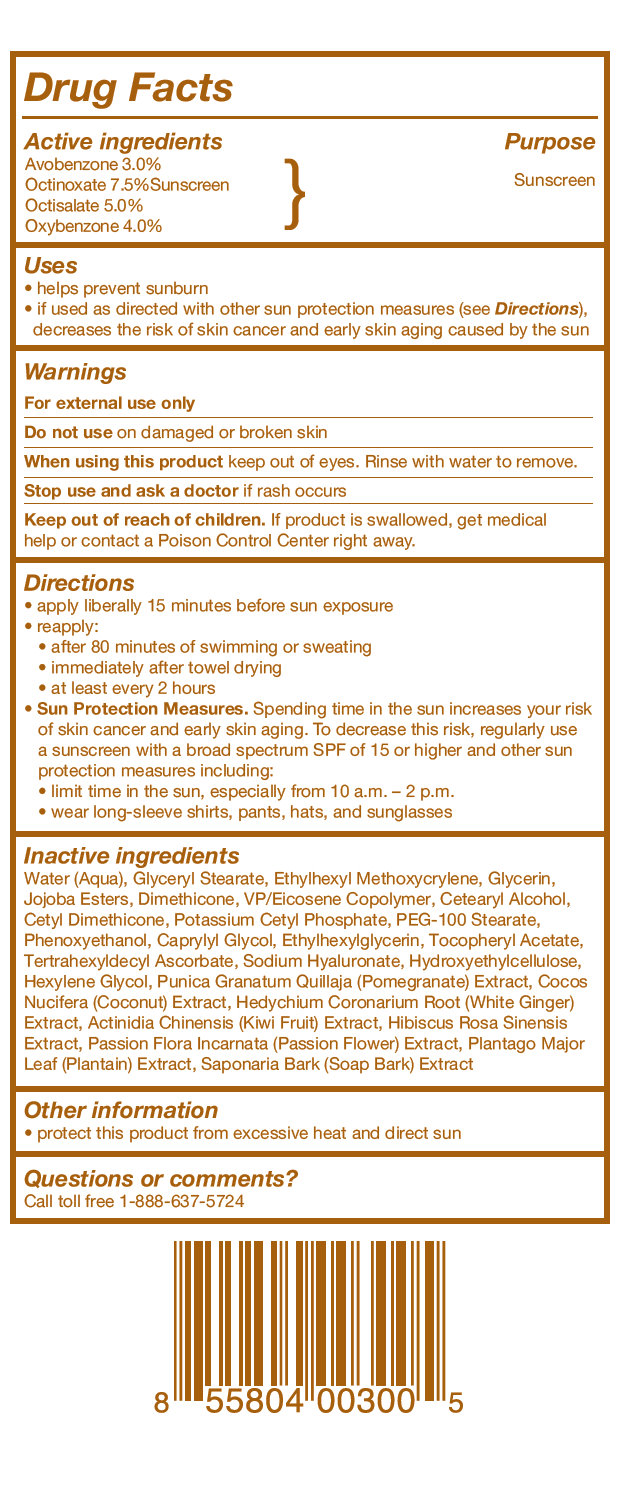 DRUG LABEL: EXTRASHADE Daily Defense Hydrating Sunscreen SPF 30
NDC: 42338-001 | Form: LOTION
Manufacturer: Extra Shade, LLC
Category: otc | Type: HUMAN OTC DRUG LABEL
Date: 20250318

ACTIVE INGREDIENTS: AVOBENZONE 30 mg/1 mL; OCTINOXATE 75 mg/1 mL; OCTISALATE 50 mg/1 mL; OXYBENZONE 40 mg/1 mL
INACTIVE INGREDIENTS: POMEGRANATE; WATER; GLYCERYL MONOSTEARATE; GLYCERIN; DIMETHICONE; CETOSTEARYL ALCOHOL; POTASSIUM CETYL PHOSPHATE; PEG-100 STEARATE; PHENOXYETHANOL; CAPRYLYL GLYCOL; ETHYLHEXYLGLYCERIN; .ALPHA.-TOCOPHEROL ACETATE, DL-; HYALURONATE SODIUM; HYDROXYETHYL CELLULOSE (2000 MPA.S AT 1%); HEXYLENE GLYCOL; COCONUT; HEDYCHIUM CORONARIUM ROOT; HIBISCUS ROSA-SINENSIS FLOWER; PASSIFLORA INCARNATA FRUIT; PLANTAGO MAJOR LEAF; QUILLAJA SAPONARIA BARK; EICOSYL POVIDONE; HYDROGENATED JOJOBA OIL/JOJOBA OIL, RANDOMIZED (IODINE VALUE 57-61); ACTINIDIA CHINENSIS (KIWI) FRUIT; ETHYLHEXYL METHOXYCRYLENE; TETRAHEXYLDECYL ASCORBATE; CETYL DIMETHICONE 45

EXTRASHADE Daily Defense Hydrating Sunscreen SPF 30 (4 fl oz / 120 ml)

Active ingredients

Active ingredients Purpose
Avobenzone 3.0%
Octinoxate 7.5%Sunscreen } Sunscreen
Octisalate 5.0%
Oxybenzone 4.0%

Uses

• helps prevent sunburn
• if used as directed with other sun protection measures (see Directions), decreases the risk of skin cancer and early skin aging caused by the sun

Warnings

For external use only

Do not use

on damaged or broken skin

When using this product

keep out of eyes. Rinse with water to remove.

Stop use and ask a doctor

if rash occurs

Keep out of reach of children. If product is swallowed, get medical help or contact a Poison Control Center right away.

Directions

• apply liberally 15 minutes before sun exposure
• reapply:
• after 80 minutes of swimming or sweating
• immediately after towel drying
• at least every 2 hours
• Sun Protection Measures. Spending time in the sun increases your risk of skin cancer and early skin aging. To decrease this risk, regularly use a sunscreen with a broad spectrum SPF of 15 or higher and other sun protection measures including:
• limit time in the sun, especially from 10 a.m. – 2 p.m.
• wear long-sleeve shirts, pants, hats, and sunglasses.

Inactive ingredients

Water (Aqua), Glyceryl Stearate, Ethylhexyl Methoxycrylene, Glycerin, Jojoba Esters, Dimethicone, VP/Eicosene Copolymer, Cetearyl Alcohol, Cetyl Dimethicone, Potassium Cetyl Phosphate, PEG-100 Stearate, Phenoxyethanol, Caprylyl Glycol, Ethylhexylglycerin, Tocopheryl Acetate, Tertrahexyldecyl Ascorbate, Sodium Hyaluronate, Hydroxyethylcellulose, Hexylene Glycol, Punica Granatum Quillaja (Pomegranate) Extract, Cocos Nucifera (Coconut) Extract, Hedychium Coronarium Root (White Ginger) Extract, Actinidia Chinensis (Kiwi Fruit) Extract, Hibiscus Rosa Sinensis Extract, Passion Flora Incarnata (Passion Flower) Extract, Plantago Major Leaf (Plantain) Extract, Saponaria Bark (Soap Bark) Extract

Other information

• protect this product from excessive heat and direct sun

Questions or comments?

Call toll free 1-888-637-5724

Purpose

Sunscreen

Description

EXTRASHADE SUN PROTECTION FOR RICH COMPLEXIONS BROAD SPECTRUM SPF 30

PACKAGE LABEL

EXTRASHADE SUN PROTECTION FOR RICH COMPLEXIONS BROAD SPECTRUM SPF 30 DAILY DEFENSE HYDRATING SUNSCREEN LOTION WATER RESISTANT (80 MINUTES) • PABA FREE FRAGRANCE FREE • OIL FREE • DYE FREE FACE AND BODY PROTECTION FOR ACTIVE LIFESTYLE 4.0 Fl Oz (120ml)

Drug Facts